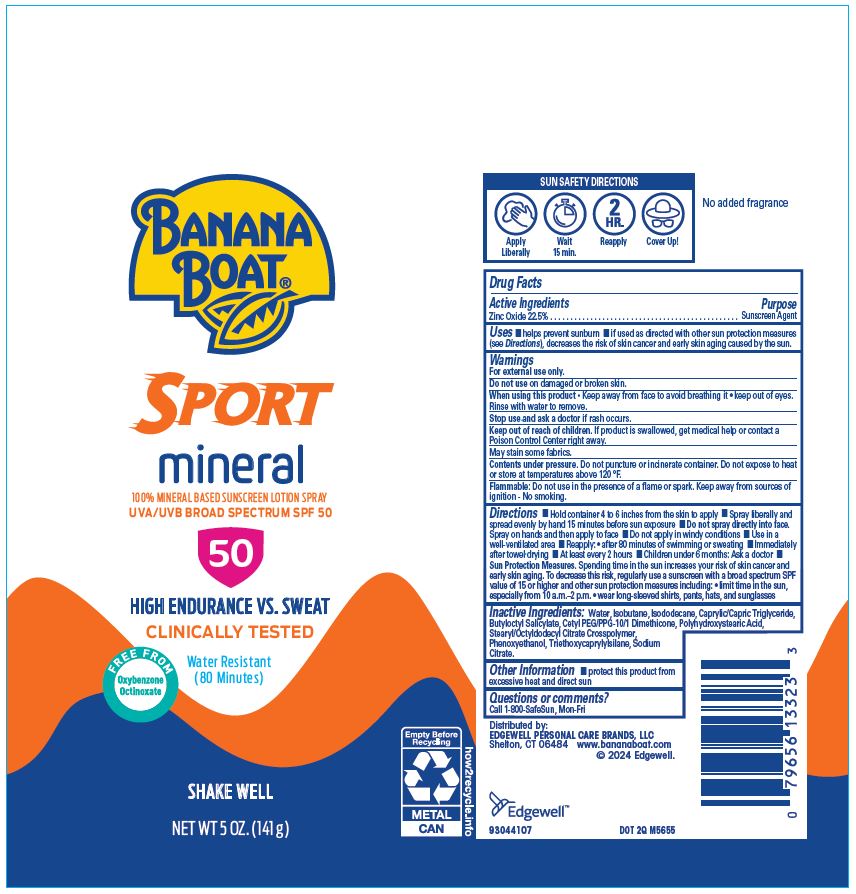 DRUG LABEL: BANANA BOAT
NDC: 63354-105 | Form: AEROSOL, SPRAY
Manufacturer: Edgewell Personal Care Brands LLC
Category: otc | Type: HUMAN OTC DRUG LABEL
Date: 20240624

ACTIVE INGREDIENTS: ZINC OXIDE 22.5 g/100 g
INACTIVE INGREDIENTS: CETYL PEG/PPG-10/1 DIMETHICONE (HLB 2); STEARYL/OCTYLDODECYL CITRATE CROSSPOLYMER; SODIUM CITRATE; WATER; POLYHYDROXYSTEARIC ACID (2300 MW); TRIETHOXYCAPRYLYLSILANE; ISOBUTANE; BUTYLOCTYL SALICYLATE; PHENOXYETHANOL; MEDIUM-CHAIN TRIGLYCERIDES; ISODODECANE

Active Ingredients

Zinc Oxide 22.5%

Purpose

Sunscreen Agent

Uses

• helps prevent sunburn • if used as directed with other sun protection measures (see Directions), decreases the risk of skin cancer and early skin aging caused by the sun.

Warnings

For external use only.

May stain some fabrics.
Contents under pressure. Do not puncture or incinerate container. Do not expose to heat or store at temperatures above 120 °F.
Flammable: Do not use in the presence of a flame or spark. Keep away from sources of ignition - No smoking.

Do not use

on damaged or broken skin.

When using this product

• Keep away from face to avoid breathing it • keep out of eyes. Rinse with water to remove.

Stop use and ask a doctor

if rash occurs.

Keep out of reach of children.

If product is swallowed, get medical help or contact a Poison Control Center right away.

Directions

Hold container 4 to 6 inches from the skin to apply • Spray liberally and spread evenly by hand 15 minutes before sun exposure • Do not spray directly into face. Spray on hands and then apply to face • Do not apply in windy conditions • Use in a well-ventilated area • Reapply: • after 80 minutes of swimming or sweating • Immediately after towel drying • At least every 2 hours • Children under 6 months: Ask a doctor •Sun Protection Measures. Spending time in the sun increases your risk of skin cancer and early skin aging. To decrease this risk, regularly use a sunscreen with a broad spectrum SPF value of 15 or higher and other sun protection measures including: • limit time in the sun, especially from 10 a.m.–2 p.m. • wear long-sleeved shirts, pants, hats, and sunglasses

Inactive Ingredients:

Water, Isobutane, Isododecane, Caprylic/Capric Triglyceride, Butyloctyl Salicylate, Cetyl PEG/PPG-10/1 Dimethicone, Polyhydroxystearic Acid, Stearyl/Octyldodecyl Citrate Crosspolymer, Phenoxyethanol, Triethoxycaprylylsilane, Sodium Citrate.

Other Information

• protect this product from excessive heat and direct sun

Questions or comments?

Call 1-800-SafeSun, Mon-Fri

Principal Display Panel

BANANA BOAT(R)
SPORT
mineral
100% MINERAL BASED SUNSCREEN LOTION SPRAY
UVA/UVB BROAD SPECTRUM SPF 50
50
HIGH ENDURANCE VS. SWEAT
CLINICALLY TESTED
FREE FROM
Oxybenzone
Octinoxate
Water Resistant
(80 Minutes)
NET WT 5 OZ. (141 g)